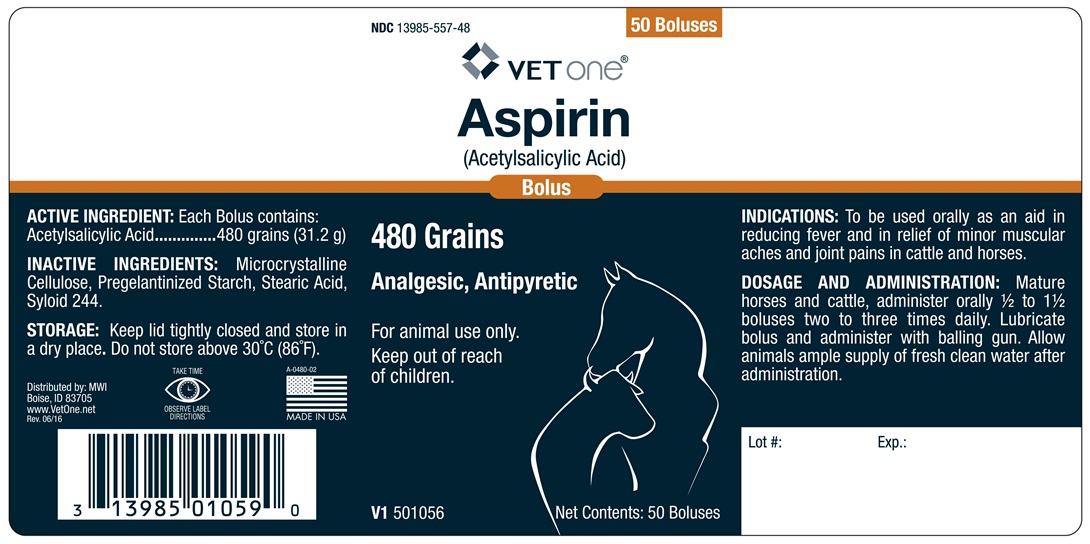 DRUG LABEL: ASPIRIN BOLUS
                        
NDC: 13985-557 | Form: TABLET
Manufacturer: MWI Veterinary Supply, Inc.
Category: animal | Type: OTC ANIMAL DRUG LABEL
Date: 20170623

ACTIVE INGREDIENTS: ASPIRIN 31.2 g/1 1

Aspirin

INDICATIONS AND USAGE

(Acetylsalicylic Acid)

480 Grains

Analgesic, Antipyretic

For animal use only.

Keep out of reach of children.

INDICATIONS

To be used orally as an aid in reducing fever and in relief of minor muscular aches and joint pains in cattle, horses.

DOSAGE AND ADMINISTRATION

Mature Horses and Cattle, administer orally 1/2 to 1 1/2 Boluses two to three times daily. Lubricate bolus and administer with balling gun. Allow Animals ample supply of fresh clean water after administration.

COMPONENTS

ACTIVE INGREDIENTS

Each Bolus contains:

Acetylsalicylic Acid..........480 grains (31.2 g)

INACTIVE INGREDIENTS

Microcrystalline Cellulose, Pregelantinized Starch, Stearic Acid, Syloid 244

STORAGE AND HANDLING

Keep lid tightly closed and store in a dry place. Do not store above 30o C (86o F).